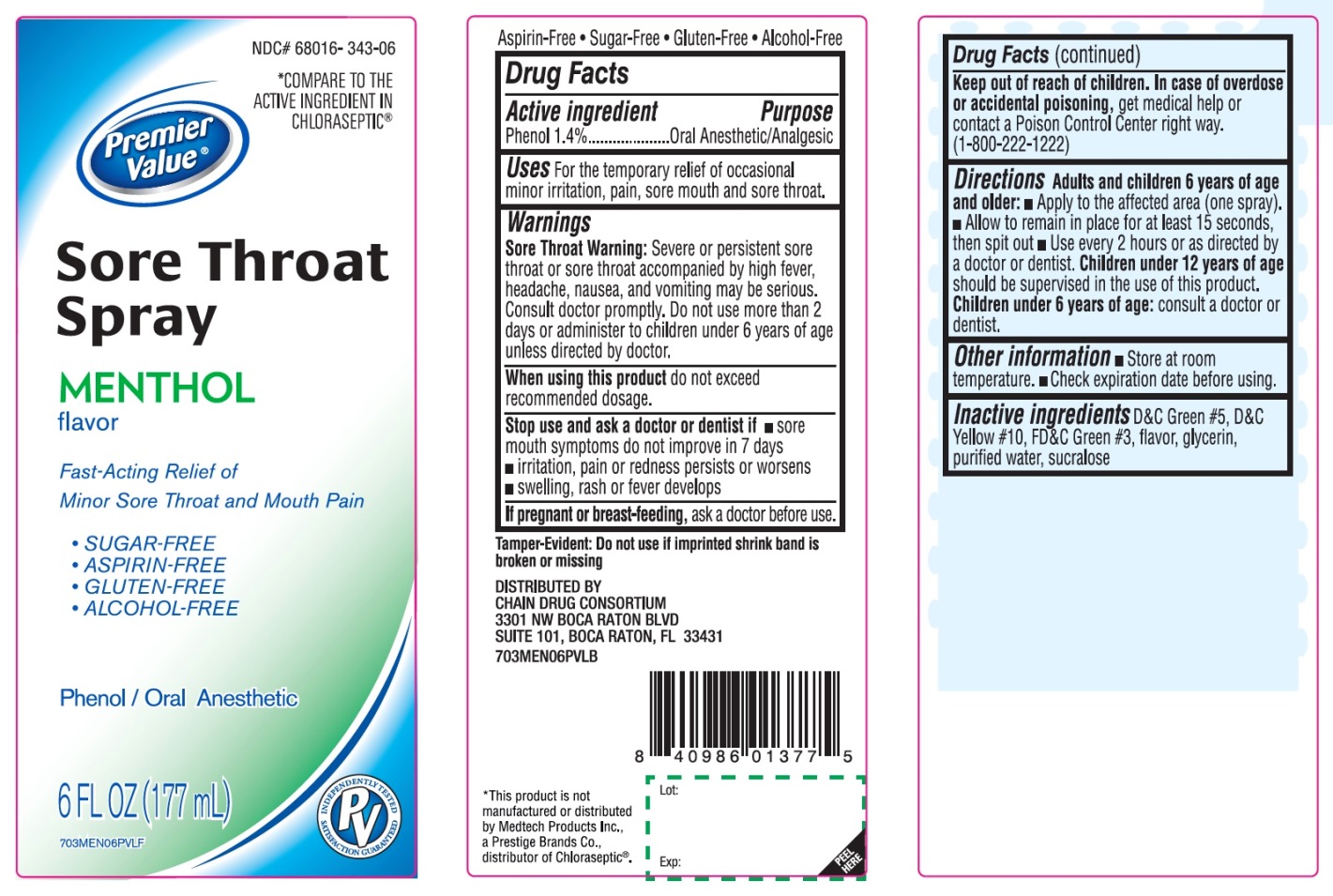 DRUG LABEL: Sore Throat Relief
NDC: 68016-343 | Form: SPRAY
Manufacturer: Chain Drug Consortium
Category: otc | Type: HUMAN OTC DRUG LABEL
Date: 20241028

ACTIVE INGREDIENTS: PHENOL 1.4 g/100 mL
INACTIVE INGREDIENTS: D&C GREEN NO. 5; D&C YELLOW NO. 10; FD&C GREEN NO. 3; GLYCERIN; WATER; SUCRALOSE

Sore Throat Spray Drug Facts

Active ingredient

Phenol 1.4%

Purpose

Oral Anesthetic/Analgesic

Uses

temporarily relieves sore throat pain, sore mouth, pain associated with canker sores, minor mouth irritation

Warnings

Sore throat warning: Severe or persistent sore throat or sore throat that occurs with high fever, headache, nausea, and vomiting may be serious. Ask a doctor right away. Do not use more than 2 days or give to children under 3 years of age.

When using this product,

do not use more than directed.

Stop use and ask a doctor if

- sore mouth symptoms do not improve in 7 days
- irritation, pain or redness persists or worsens
- swelling, rash or fever develops

If pregnant or breast-feeding,

ask a doctor before use.

Keep out of reach of children.

In case of overdose or accidental poisoning, get medical help or contact a Poison Control Center right away (1-800-222-1222)

Directions

Adults and children 6 years of age and older:

- Apply to the affected area (one spray)
- Allow to remain in place for at least 15 seconds, then spit out
- Use every 2 hours or as directed by a doctor
Children under 12 years of age should be supervised in the use of this product
Children under 6 years of age: consult a doctor or dentist

Other information

- Store at room temperature
- Check expiration date before using

Inactive ingredients

D&C Green #5, D&C Yellow #10, FD&C Green #3, flavor, glycerin, purified water, sucralose

Principal Display Panel

*Compare to the active ingredient in Chloraseptic®*

Sore Throat Relief

Menthol Flavor

Fast acting relief of Minor Sore Throat and Mouth Pain

Phenol/Oral Anesthetic

Sugar-Free

Aspirin-Free

Gluten-Free

Alcohol-Free

6 FL OZ (177 mL)

*This product is not manufactured or distributed by Medtech Products Inc., a Prestige Brands Co., distributor of Chloraseptic®.

Tamper-Evident: Do not use if imprinted shrink band is broken or missing.

DISTRIBUTED BY:

Chain Drug Consortium LLC.

3301 N.W. Boca Raton Blvd.

Suite 101, Boca Raton FL 33431